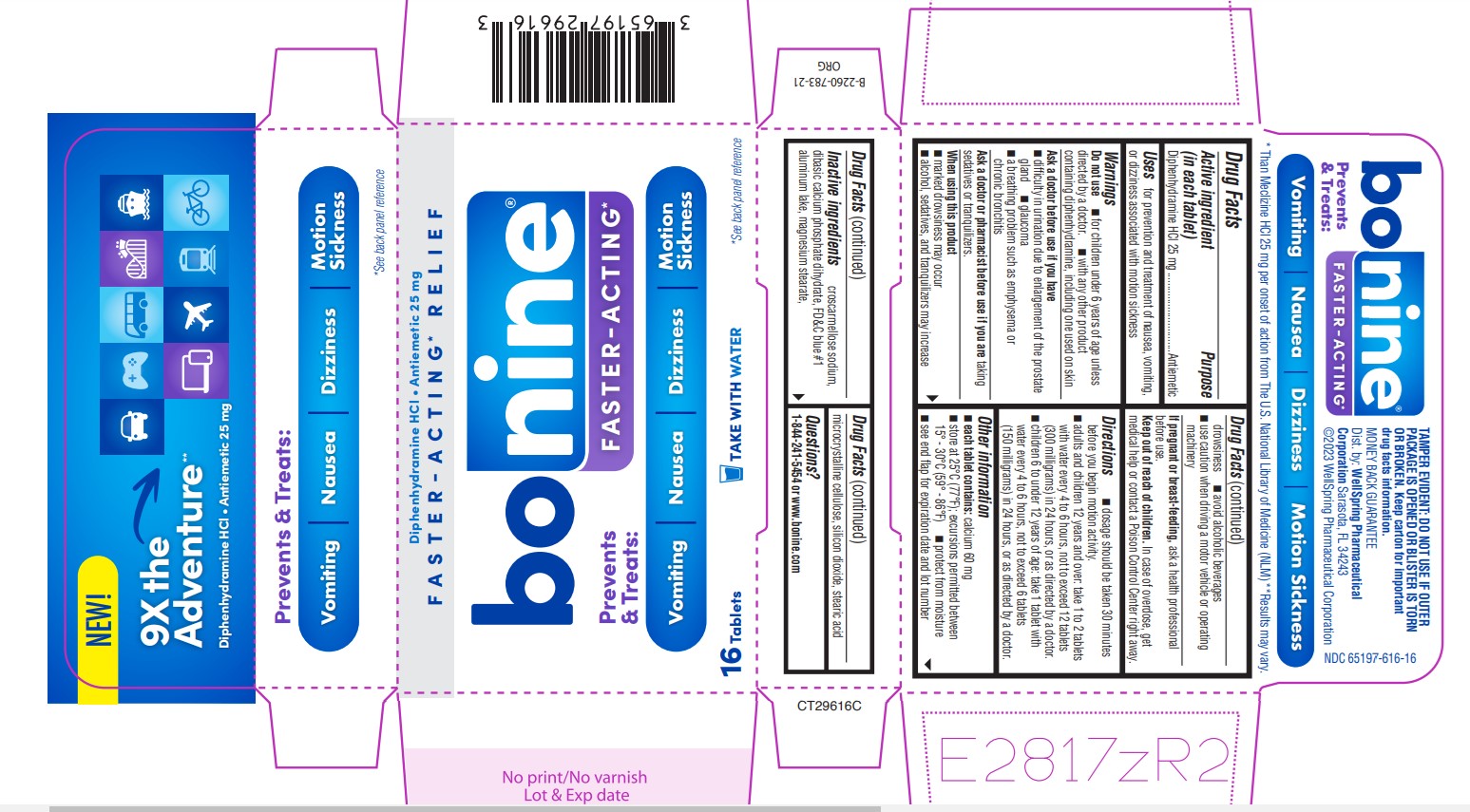 DRUG LABEL: BONINE
NDC: 65197-616 | Form: TABLET
Manufacturer: WellSpring Pharmaceutical Corporation
Category: otc | Type: HUMAN OTC DRUG LABEL
Date: 20220706

ACTIVE INGREDIENTS: DIPHENHYDRAMINE HYDROCHLORIDE 25 mg/1 1
INACTIVE INGREDIENTS: CROSCARMELLOSE SODIUM; DIBASIC CALCIUM PHOSPHATE DIHYDRATE; FD&C BLUE NO. 1 ALUMINUM LAKE; MAGNESIUM STEARATE; MICROCRYSTALLINE CELLULOSE 101; SILICON DIOXIDE; STEARIC ACID

BONINE®
MECLIZINE HYDROCHLORIDE • ANTIEMETIC

Active ingredient (in each tablet)

Diphenhydramine HCl 25 mg

Purpose

Antiemetic

Uses

for prevention and treatment of nausea, vomiting, Uses or dizziness associated with motion sickness

Warnings

Do not use

■ for children under 6 years of age unless

■ Do not use with any other product containing diphenhydramine, including one used on skin

Ask a doctor before use if you have

■ difficulty in urination due to enlargement of the prostate gland

■ glaucoma

■ difficulty in urination due to enlargement of the prostate gland

Ask a doctor or pharmacist before use if you are

taking sedatives or tranquilizers.

When using this product

■ marked drowsiness may occur

■ alcohol, sedatives, and tranquilizers may increase drowsiness

■ avoid alcoholic beverages

■ use caution when driving a motor vehicle or operating machinery

If pregnant or breast-feeding

ask a health professional before use.

Keep out of reach of children

In case of overdose, get medical help or contact a Poison Control Center right away.

Directions

■ dosage should be taken 30 minutes before you begin motion activity.

■ adults and children 12 years and over: take 1 to 2 tablets with Water every 4 to 6 hours, not to exceed 12 tablets (300 milligrams) in 24 hours, or as directed by a doctor.

■ Children 6 to under 12 years of age: take 1 tablet with Water every 4 to 6 hours, not to exceed 6 tablets (150 milligrams) in 24 hours, or as directed by a doctor.

Other information

■ Each tablet contains: Calcium 60mg

■ Store at 25°C (77°F); excursions permitted between 15° - 30°C (59° - 86°F)

■ protect from moisture

■ see end flap for expiration date and lot number

Inactive ingredients

Croscarmellose sodium, dibasic calcium phosphate dihydrate, FD&C blue #1, aluminum lake, magnesium stearate, microcrystalline cellulose, silicone dioxide, stearic acid

Questions?

1-844-241-5454 or www.bonine.com

TAMPER EVIDENT: DO NOT USE IF OUTER PACKAGE IS OPENED OR BLISTER IS TORN OR BROKEN. Keep Carton for important drug facts information.

Distributed by: WellSpring
Pharmaceutical Corporation
Sarasota, FL 34243
©2023 WellSpring
Pharmaceutical Corporation

Money Back Guarantee

PRINCIPAL DISPLAY PANEL 65197-616-16

NEW

9X the Adventure**

Diphenhydramine HCl - Antiemetic 25 mg

Prevents & Treats:

Vomiting • Nausea • Dizziness • Motion Sickness

*See back panel reference

* Than Meclizine HCL 25 mg per onset of action from The U.S. National Library of Medicine (NLM)

** Results may vary

FASTER-ACTING* RELIEF

TAKE WITH WATER

Bonine Faster Acting 2.0